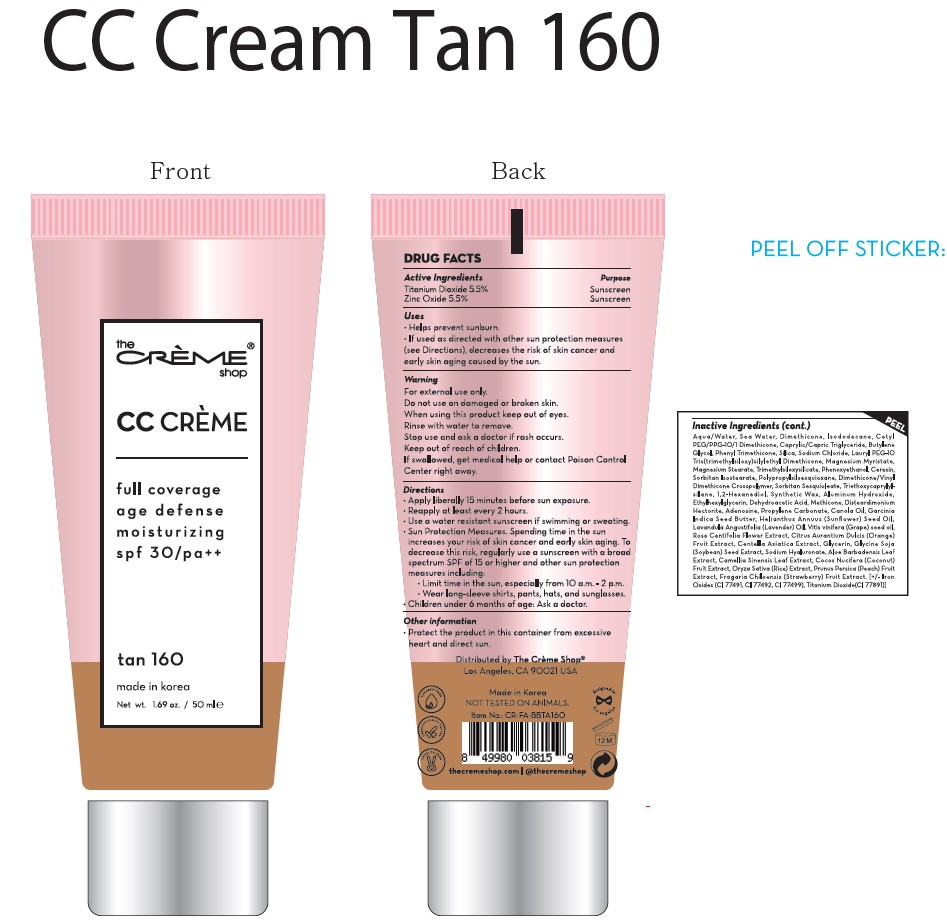 DRUG LABEL: CC Cream Tan160
NDC: 81123-328 | Form: CREAM
Manufacturer: The Creme Shop Inc
Category: otc | Type: HUMAN OTC DRUG LABEL
Date: 20220503

ACTIVE INGREDIENTS: TITANIUM DIOXIDE 5.5 mg/100 mg; ZINC OXIDE 5.5 mg/100 mg
INACTIVE INGREDIENTS: WATER; ISODODECANE; FERRIC OXIDE YELLOW; MEDIUM-CHAIN TRIGLYCERIDES; PHENOXYETHANOL; TRIETHOXYCAPRYLYLSILANE; CERESIN; MAGNESIUM STEARATE; 1,2-HEXANEDIOL; SYNTHETIC WAX (1200 MW); DIMETHICONE/VINYL DIMETHICONE CROSSPOLYMER (SOFT PARTICLE); DEHYDROACETIC ACID; GRAPE SEED OIL; ROSA CENTIFOLIA FLOWER; ORANGE; SOYBEAN; BEACH STRAWBERRY; FERROSOFERRIC OXIDE; SORBITAN ISOSTEARATE; SUNFLOWER OIL; RICE GERM; PROPYLENE CARBONATE; GARCINIA INDICA SEED BUTTER; ALOE VERA LEAF; PEACH; SODIUM CHLORIDE; ETHYLHEXYLGLYCERIN; COCONUT; HYALURONATE SODIUM; METHICONE (20 CST); FERRIC OXIDE RED; BUTYLENE GLYCOL; DISTEARDIMONIUM HECTORITE; ADENOSINE; CANOLA OIL; LAVENDER OIL; CENTELLA ASIATICA; GLYCERIN; GREEN TEA LEAF; LAURYL PEG-9 POLYDIMETHYLSILOXYETHYL DIMETHICONE; DIMETHICONE; CETYL PEG/PPG-10/1 DIMETHICONE (HLB 2); PHENYL TRIMETHICONE; SILICON DIOXIDE; MAGNESIUM MYRISTATE; SORBITAN SESQUIOLEATE; ALUMINUM HYDROXIDE

81123-328 Tan160

Active Ingredient

Titanium Dioxide 5.5%
Zinc Oxide 5.5%

Purpose

Helps prevent sunburn.

Uses

If uses as directed with other sun protection measures(see Directions), decreases the risk of skin cancer and early skin aging caused by the sun.

Warnings

For external use only.
Rinse with water to remove.
If swallowed, get medical help or contact Poison Control Center right away.

Warnings

Do not use on damaged or broken skin.

Warnings

Keep out of reach of children.

Warnings

Stop use and ask a doctor if rash occurs.

Directions

Apply liberally 15 minutes before sun exposure.
Reapply at least every 2 hours.
Use a water resistant sunscreen if swimming or sweating.
Sun Protection Measures. Spending time in the sun increases your risk of skin cancer and early skin aging. To decrease this risk, regularly use a sunscreen with a broad spectrum SPF of 15 of higher and other sun protection measures including:
Limit time in the sun, especially from 10 a.m. - 2 p.m.
Wear long-sleeve shirts, pants, hats, and sunglasses.
Children under 6months of age: Ask a doctor.

Other Information

Protect the product in this container from excessive heart and direct sun.

Inactive Ingredient

Water, Sea Water, Dimethicone, Isododecane, Iron Oxide Yellow, Caprylic/Capric Triglyceride, Cetyl PEG/PPG-10/1 Dimethicone, Phenyl Trimethicone, Iron Oxide Red, Sodium Chloride, Butylene Glycol, Lauryl PEG-9 Polydimethylsiloxyethyl Dimethicone, Iron Oxide Black, Phenoxyethanol, Sorbitan Isostearate, Triethoxycaprylylsilane, Ceresin, Silica, Magnesium Myristate, Magnesium Stearate, Sorbitan Sesquioleate, 1,2-Hexanediol, Synthetic Wax, Dimethicone/Vinyl Dimethicone Crosspolymer, Aluminum Hydroxide, Ethylhexylglycerin, Dehydroacetic Acid, Disteardimonium Hectorite, Methicone, Adenosine, Propylene Carbonate, Canola Oil, Garcinia Indica Seed Butter, Helianthus Annuus (Sunflower) Seed Oil, Lavandula Angustifolia (Lavender) Oil, Vitis vinifera (Grape) seed oil, Rose Centifolia Flower Extract, Citrus Aurantium Dulcis (Orange) Fruit Extract, Centella Asiatica Extract, Glycerin, Glycine Soja (Soybean) Seed Extract, Aloe Barbadensis Leaf Extract, Camellia Sinensis Leaf Extract, Cocos Nucifera (Coconut) Fruit Extract, Oryza Sativa (Rice) Extract, Prunus Persica (Peach) Fruit Extract, Fragaria Chiloensis (Strawberry) Fruit Extract, Sodium Hyaluronate